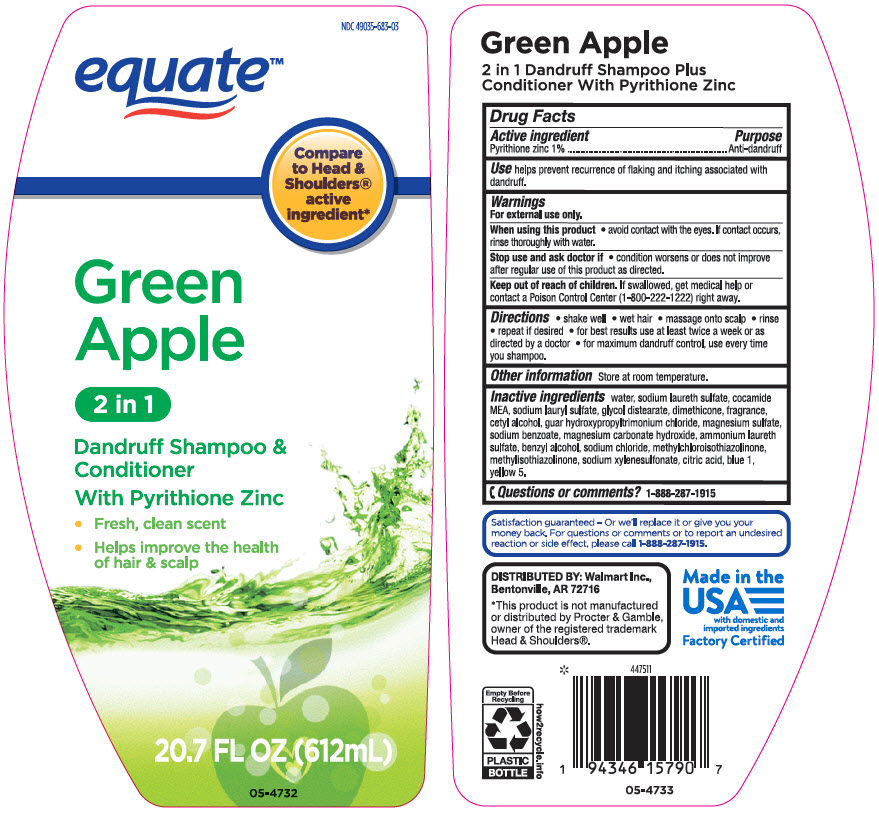 DRUG LABEL: Equate Green Apple 2 in 1 Dandruff
NDC: 49035-683 | Form: SHAMPOO
Manufacturer: Wal-Mart Stores, Inc.
Category: otc | Type: HUMAN OTC DRUG LABEL
Date: 20231215

ACTIVE INGREDIENTS: Pyrithione Zinc 10 mg/1 mL
INACTIVE INGREDIENTS: Water; SODIUM LAURETH-3 SULFATE; COCO MONOETHANOLAMIDE; Sodium Lauryl Sulfate; Glycol Distearate; Dimethicone; Cetyl Alcohol; GUAR HYDROXYPROPYLTRIMONIUM CHLORIDE (1.7 SUBSTITUENTS PER SACCHARIDE); MAGNESIUM SULFATE, UNSPECIFIED FORM; Sodium Benzoate; Magnesium Carbonate Hydroxide; AMMONIUM LAURETH-5 SULFATE; Benzyl Alcohol; Sodium Chloride; Methylchloroisothiazolinone; Methylisothiazolinone; Sodium Xylenesulfonate; CITRIC ACID MONOHYDRATE; FD&C BLUE NO. 1; FD&C YELLOW NO. 5

Equate™ Green Apple 2 in 1 Dandruff Shampoo & Conditioner
Anti-Dandruff

Drug Facts

Active ingredient

Pyrithione Zinc 1%

Purpose

Anti-dandruff

Use

helps prevent recurrence of flaking and itching associated with dandruff.

Warnings

For external use only

When using this product

- avoid contact with the eyes. If contact occurs, rinse eyes thoroughly with water

Stop use and ask a doctor if

- condition worsens or does not improve after regular use of this product as directed

Keep out of reach of children. If swallowed, get medical help or contact a Poison Control Center right away

Directions

- shake well
- wet hair
- massage onto scalp
- rinse
- repeat if desired
- for best results use at least twice a week or as directed by a doctor
- for maximum dandruff control, use every time you shampoo

Other information

store at room temperature

Inactive ingredients

water, sodium laureth sulfate, cocamide MEA, sodium lauryl sulfate, glycol distearate, dimethicone, fragrance, cetyl alcohol, guar hydroxypropyltrimonium chloride, magnesium sulfate, sodium benzoate, magnesium carbonate hydroxide, ammonium laureth sulfate, benzyl alcohol, sodium chloride, methylchloroisothiazolinone, methylisothiazolinone, sodium xylenesulfonate, citric acid, blue 1, yellow 5

QUESTIONS

Satisfaction guaranteed – For questions or comments please call 1-888-287-1915.

DISTRIBUTED BY: Wal-Mart Stores, Inc.,
Bentonville, AR 72716

PRINCIPAL DISPLAY PANEL - 612 mL Bottle Label

NDC 49035-683-03

equate™

Compare
to Head &
Shoulders®
active
ingredient*

Green
Apple

2 in 1

Dandruff Shampoo &
Conditioner

With Pyrithione Zinc

- Fresh, clean scent
- Helps improve the health
  of hair & scalp

20.7 FL OZ (612mL)

05-4732